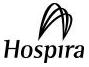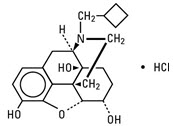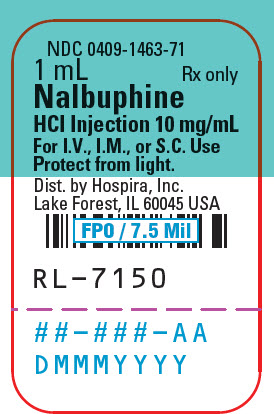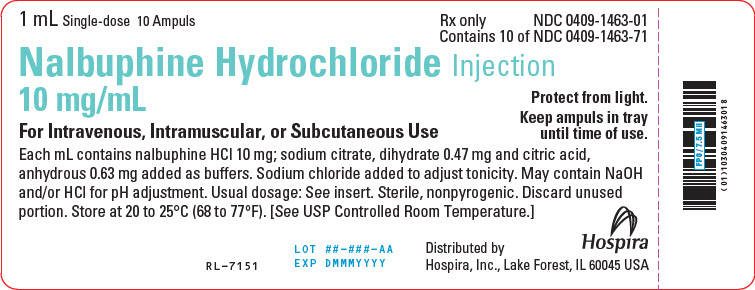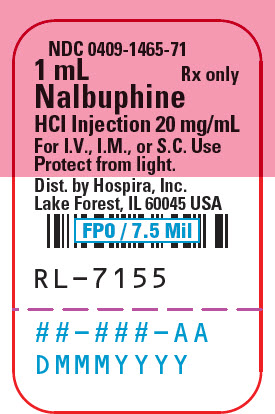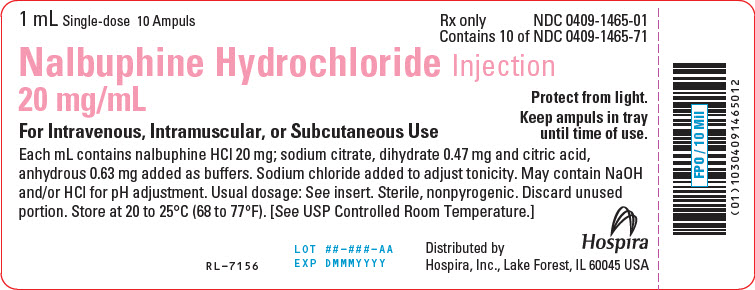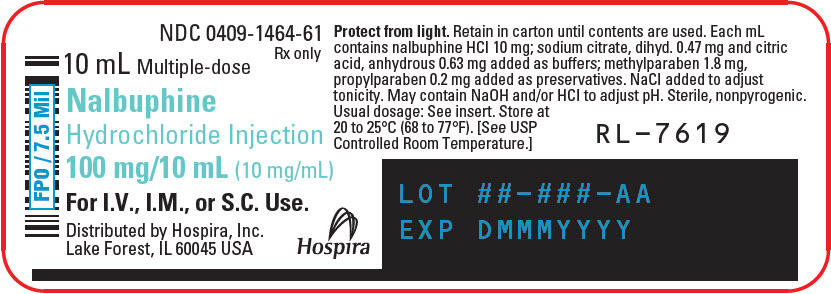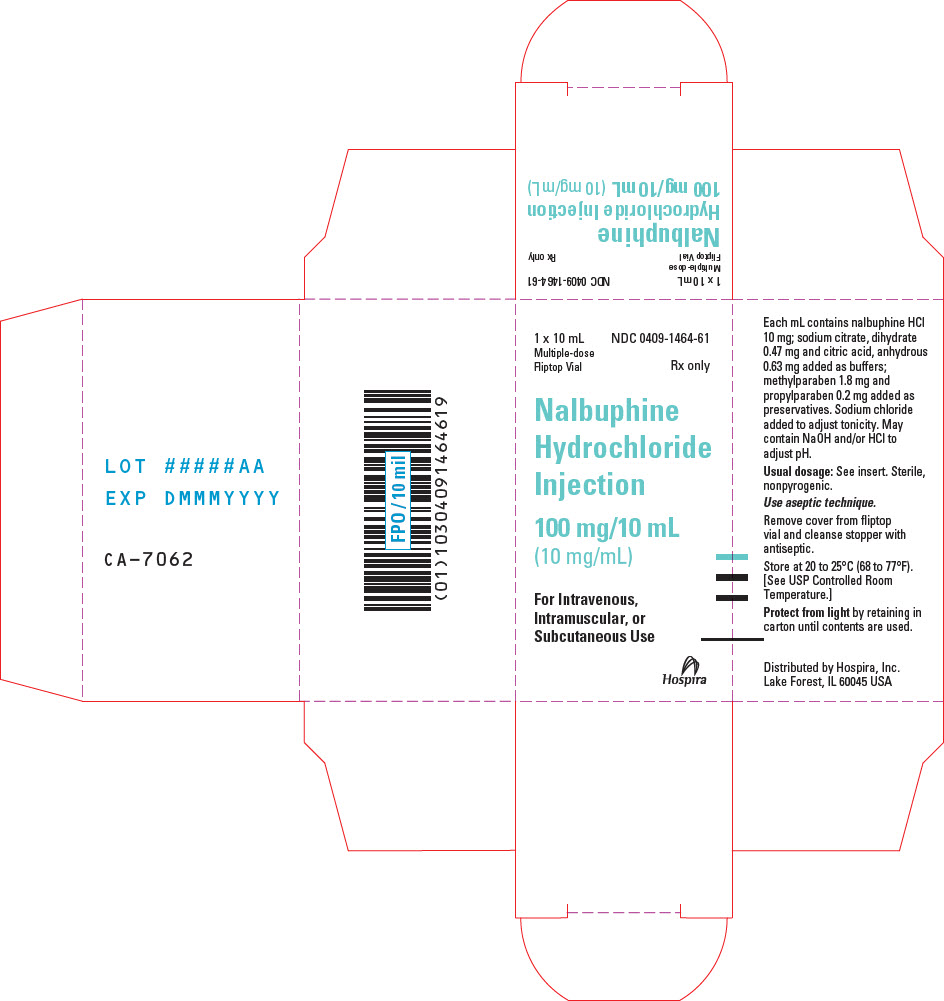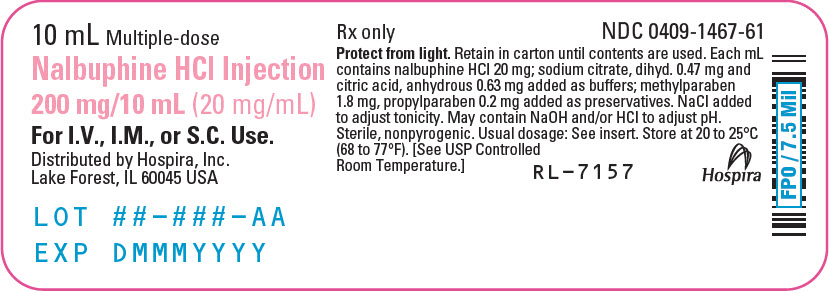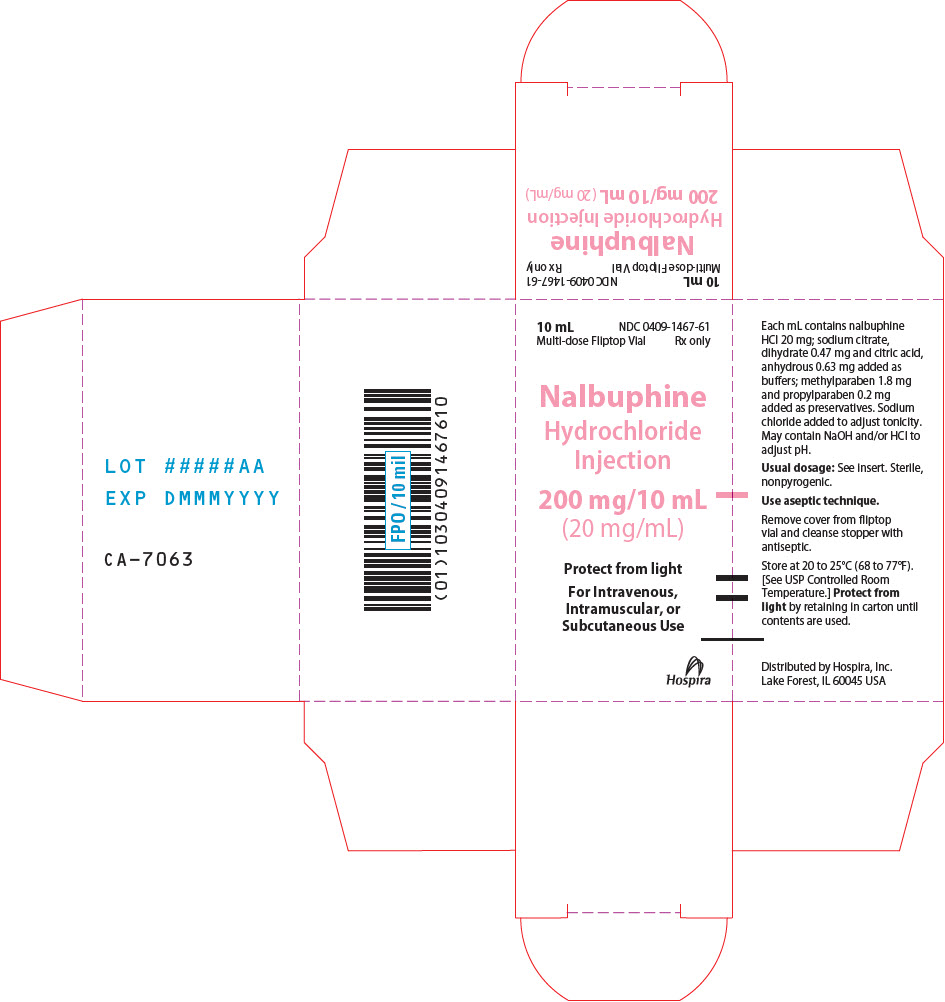 DRUG LABEL: Nalbuphine Hydrochloride
NDC: 0409-1463 | Form: INJECTION, SOLUTION
Manufacturer: Hospira, Inc.
Category: prescription | Type: HUMAN PRESCRIPTION DRUG LABEL
Date: 20251231

ACTIVE INGREDIENTS: NALBUPHINE HYDROCHLORIDE 10 mg/1 mL
INACTIVE INGREDIENTS: TRISODIUM CITRATE DIHYDRATE 0.47 mg/1 mL; ANHYDROUS CITRIC ACID 0.63 mg/1 mL; SODIUM CHLORIDE; SODIUM HYDROXIDE; HYDROCHLORIC ACID; WATER

NALBUPHINE HYDROCHLORIDE

Injection
Ampul
Fliptop Vial
Protect from light.

Rx only

WARNING: SERIOUS AND LIFE-THREATENING RISKS FROM USE OF NALBUPHINE HYDROCHLORIDE INJECTION

‎Addiction, Abuse, and Misuse

Because the use of Nalbuphine Hydrochloride Injection exposes patients and other users to the risks of opioid addiction, abuse, and misuse, which can lead to overdose and death, assess each patient's risk prior to prescribing and reassess all patients regularly for the development of these behaviors and conditions [see WARNINGS].

Life-Threatening Respiratory Depression

Serious, life-threatening, or fatal respiratory depression may occur with use of Nalbuphine Hydrochloride Injection, especially during initiation or following a dosage increase. To reduce the ‎risk of respiratory depression, proper dosing, and titration of ‎‎Nalbuphine Hydrochloride Injection are essential [see WARNINGS].

Risks From Concomitant Use With Benzodiazepines Or Other CNS Depressants

Concomitant use of opioids with benzodiazepines or other central nervous system (CNS) depressants, including alcohol, may result in profound sedation, respiratory depression, coma, and death. Reserve concomitant prescribing of Nalbuphine Hydrochloride Injection and benzodiazepines or other CNS depressants for use in patients for whom alternative treatment options are inadequate [see WARNINGS, PRECAUTIONS; Drug Interactions].

DESCRIPTION

Nalbuphine hydrochloride is a synthetic opioid agonist-antagonist analgesic of the phenanthrene series. It is chemically related to both the widely used opioid antagonist, naloxone, and the potent opioid analgesic, oxymorphone. Chemically nalbuphine hydrochloride is 17-(cyclobutylmethyl)-4,5α-epoxymorphinan-3,6α,14-triol hydrochloride. Nalbuphine hydrochloride molecular weight is 393.91 and is soluble in H2O (35.5 mg/mL at 25ºC) and ethanol (0.8%); insoluble in CHCl3 and ether. Nalbuphine hydrochloride has pKa values of 8.71 and 9.96. The molecular formula is C21H27NO4 ∙ HCl. The structural formula is:

Nalbuphine Hydrochloride Injection is a sterile, nonpyrogenic solution of nalbuphine hydrochloride in water for injection. This product may be administered by subcutaneous, intramuscular, or intravenous injection.

Each milliliter (mL) contains nalbuphine hydrochloride 10 mg or 20 mg; sodium citrate, dihydrate 0.47 mg and citric acid, anhydrous 0.63 mg added as buffers and may contain sodium hydroxide and/or hydrochloric acid for pH adjustment; pH 3.7 (3.0 to 4.5). Contains sodium chloride for tonicity adjustment.

Multiple-dose vials contain 1.8 mg/mL methylparaben and 0.2 mg/mL propylparaben added as preservatives. Single-dose products contain no bacteriostat or antimicrobial agent and unused portions must be discarded.

CLINICAL PHARMACOLOGY

Mechanism of Action

Nalbuphine is an agonist at kappa opioid receptors and an antagonist at mu opioid receptors.

Pharmacodynamics

Nalbuphine Hydrochloride Injection is a potent analgesic. Its analgesic potency is essentially equivalent to that of morphine on a milligram basis up to a dosage of approximately 30 mg.

The opioid antagonist activity of Nalbuphine Hydrochloride Injection is one-fourth as potent as nalorphine and 10 times that of pentazocine.

Nalbuphine Hydrochloride Injection may produce the same degree of respiratory depression as equianalgesic doses of morphine. However, Nalbuphine Hydrochloride Injection exhibits a ceiling effect such that increases in dose greater than 30 mg do not produce further respiratory depression in the absence of other CNS active medications affecting respiration.

Nalbuphine Hydrochloride Injection by itself has potent opioid antagonist activity at doses equal to or lower than its analgesic dose. When administered following or concurrent with mu agonist opioid analgesics (e.g., morphine, oxymorphone, fentanyl), nalbuphine hydrochloride may partially reverse or block opioid-induced respiratory depression from the mu agonist analgesic. Nalbuphine Hydrochloride Injection may precipitate withdrawal in patients dependent on opioid drugs. Nalbuphine Hydrochloride Injection should be used with caution in patients who have been receiving mu opioid analgesics on a regular basis.

Effects on the Central Nervous System

Nalbuphine produces respiratory depression by direct action on brain stem respiratory centers. The respiratory depression involves a reduction in the responsiveness of the brain stem respiratory centers to both increases in carbon dioxide tension and electrical stimulation. However, there may be a ceiling effect for the respiratory depression caused by nalbuphine. Although a mixed agonist/antagonist, the respiratory depressant effects of nalbuphine can be reversed by naloxone.

Nalbuphine causes miosis, even in total darkness. Pinpoint pupils are a sign of opioid overdose but are not pathognomonic (e.g., pontine lesions of hemorrhagic or ischemic origins may produce similar findings). Marked mydriasis rather than miosis may be seen due to hypoxia in overdose situations.

Effects on the Gastrointestinal Tract and Other Smooth Muscle

Nalbuphine causes a reduction in motility associated with an increase in smooth muscle tone in the antrum of the stomach and duodenum. Digestion of food in the small intestine is delayed and propulsive contractions are decreased. Propulsive peristaltic waves in the colon are decreased, while tone may be increased to the point of spasm, resulting in constipation. Other opioid-induced effects may include a reduction in biliary and pancreatic secretions, spasm of sphincter of Oddi, transient elevations in serum amylase, and opioid-induced esophageal dysfunction (OIED).

Effects on the Cardiovascular System

During use of nalbuphine during anesthesia, a higher incidence of bradycardia has been reported in patients who did not receive atropine pre-operatively.

Opioids produce peripheral vasodilation, which may result in orthostatic hypotension or syncope. Manifestations of histamine release and/or peripheral vasodilation may include pruritus, flushing, red eyes, sweating, and/or orthostatic hypotension.

Effects on the Endocrine System

Opioids inhibit the secretion of adrenocorticotropic hormone (ACTH), cortisol, and luteinizing hormone (LH) in humans [see ADVERSE REACTIONS]. They also stimulate prolactin, growth hormone (GH) secretion, and pancreatic secretion of insulin and glucagon.

Use of opioids for an extended period of time may influence the hypothalamic-pituitary-gonadal axis, leading to androgen deficiency that may manifest as low libido, impotence, erectile dysfunction, amenorrhea, or infertility.

The causal role of opioids in the clinical syndrome of hypogonadism is unknown because the various medical, physical, lifestyle, and psychological stressors that may influence gonadal hormone levels have not been adequately controlled for in studies conducted to date [see ADVERSE REACTIONS].

Effects on the Immune System

Opioids have been shown to have a variety of effects on components of the immune system in in vitro and animal models. The clinical significance of these findings is unknown. Overall, the effects of opioids appear to be modestly immunosuppressive.

Concentration–Efficacy Relationships

The minimum effective analgesic concentration will vary widely among patients, especially among patients who have been previously treated with extended-release opioid agonists. The minimum effective analgesic concentration of nalbuphine for any individual patient may increase over time due to an increase in pain, the development of a new pain syndrome, and/or the development of analgesic tolerance [see DOSAGE AND ADMINISTRATION].

Pharmacokinetics

The onset of action of Nalbuphine Hydrochloride Injection occurs within 2 to 3 minutes after intravenous administration, and in less than 15 minutes following subcutaneous or intramuscular injection. The plasma half-life of nalbuphine is 5 hours, and in clinical studies the duration of analgesic activity has been reported to range from 3 to 6 hours.

The metabolic pathway for nalbuphine has not been defined but is likely hepatic.

INDICATIONS AND USAGE

Nalbuphine Hydrochloride Injection is indicated for the management of pain severe enough to require an opioid analgesic and for which alternative treatments are inadequate. Nalbuphine Hydrochloride Injection can also be used as a supplement to balanced anesthesia, for preoperative and postoperative analgesia, and for obstetrical analgesia during labor and delivery.

Limitations of Use:

Because of the risks of addiction, abuse, misuse, overdose, and death, which can occur at any dosage or duration and persist over the course of therapy [see WARNINGS], reserve opioid analgesics, including Nalbuphine Hydrochloride Injection, for use in patients for whom alternative treatment options are ineffective, not tolerated, or would be otherwise inadequate to provide sufficient management of pain. ‎

CONTRAINDICATIONS

Nalbuphine Hydrochloride Injection is contraindicated in patients with:

- Significant respiratory depression [see WARNINGS]
- Acute or severe bronchial asthma in an unmonitored setting or in the absence of resuscitative equipment [see WARNINGS]
- Known or suspected gastrointestinal obstruction, including paralytic ileus [see WARNINGS]
- Hypersensitivity to nalbuphine or any of the other ingredients in Nalbuphine Hydrochloride Injection.

WARNINGS

Addiction, Abuse, and Misuse

Nalbuphine Hydrochloride Injection contains nalbuphine. As an opioid, nalbuphine exposes users to the risks of addiction, abuse, and misuse [see DRUG ABUSE AND DEPENDENCE]. The risk of opioid‑related overdose or overdose-related death is increased with higher opioid doses, and this risk persists over the course of therapy. In postmarketing studies, addiction, abuse, misuse, and fatal and non-fatal opioid overdose were observed in patients with long-term opioid use [see ADVERSE REACTIONS].

Opioids are sought for non-medical use and are subject to diversion from legitimate prescribed use. Consider these risks when handling Nalbuphine Hydrochloride Injection. Strategies to reduce these risks include proper product storage and control practices for a C-II drug. Contact local state professional licensing board or state-controlled substances authority for information on how to prevent and detect abuse or diversion of this product.

Life-Threatening Respiratory Depression

Serious, life-threatening, or fatal respiratory depression has been reported with the use of opioids, even when used as recommended. Respiratory depression, if not immediately recognized and treated, may lead to respiratory arrest and death. Management of respiratory depression may include close observation, supportive measures, and use of opioid overdose reversal agents (e.g., naloxone, nalmefene), depending on the patient's clinical status [see OVERDOSAGE]. Carbon dioxide (CO2) retention from opioid-induced respiratory depression can exacerbate the sedating effects of opioids.

While serious, life-threatening, or fatal respiratory depression can occur at any time during the use of Nalbuphine Hydrochloride Injection, the risk is greatest during the initiation of therapy or following a dosage increase. Monitor patients closely for respiratory depression, especially within the first 24 to 72 hours of initiating therapy with and following dosage increases of Nalbuphine Hydrochloride Injection.

To reduce the risk of respiratory depression, proper dosing and titration of Nalbuphine Hydrochloride Injection are essential [see DOSAGE AND ADMINISTRATION]. Overestimating the Nalbuphine Hydrochloride Injection dosage when converting patients from another opioid product can result in a fatal overdose with the first dose.

Opioids can cause sleep-related breathing disorders including central sleep apnea (CSA) and sleep-related hypoxemia. Opioid use increases the risk of CSA in a dose-dependent fashion. In patients who present with CSA, consider decreasing the opioid dosage using best practices for opioid taper [see DOSAGE AND ADMINISTRATION].

Risks from Concomitant Use with Benzodiazepines or Other CNS Depressants

Profound sedation, respiratory depression, coma, and death may result from the concomitant use of Nalbuphine Hydrochloride Injection with benzodiazepines and/or other CNS depressants, including alcohol (e.g., non-benzodiazepine sedatives/hypnotics, anxiolytics, tranquilizers, muscle relaxants, general anesthetics, antipsychotics, gabapentinoids [gabapentin or pregabalin], and other opioids). Because of these risks, reserve concomitant prescribing of these drugs for use in patients for whom alternative treatment options are inadequate. Monitor patients closely for signs and symptoms of respiratory depression and sedation.

Observational studies have demonstrated that concomitant use of opioid analgesics and benzodiazepines increases the risk of drug-related mortality compared to use of opioid analgesics alone. Because of similar pharmacological properties, it is reasonable to expect similar risk with the concomitant use of other CNS depressant drugs with opioid analgesics [see PRECAUTIONS; Drug Interactions].

If the decision is made to prescribe a benzodiazepine or other CNS depressant concomitantly with an opioid analgesic, prescribe the lowest effective dosages and minimum durations of concomitant use. In patients already receiving an opioid analgesic, prescribe a lower initial dose of the benzodiazepine or other CNS depressant than indicated in the absence of an opioid, and titrate based on clinical response. If an opioid analgesic is initiated in a patient already taking a benzodiazepine or other CNS depressant, prescribe a lower initial dose of the opioid analgesic, and titrate based on clinical response. Follow patients closely for signs and symptoms of respiratory depression and sedation.

Advise both patients and caregivers about the risks of respiratory depression and sedation when Nalbuphine Hydrochloride Injection is used with benzodiazepines or other CNS depressants (including alcohol and illicit drugs). Advise patients not to drive or operate heavy machinery until the effects of concomitant use of the benzodiazepine or other CNS depressant have been determined. Screen patients for risk of substance use disorders, including opioid abuse and misuse, and warn them of the risk for overdose and death associated with the use of additional CNS depressants including alcohol and illicit drugs [see PRECAUTIONS; Drug Interactions and Information for Patients].

Opioid-Induced Hyperalgesia and Allodynia

Opioid-Induced Hyperalgesia (OIH) occurs when an opioid analgesic ‎paradoxically causes an increase in pain, or an increase in sensitivity to ‎pain. This condition differs from tolerance, which is the need for ‎increasing doses of opioids to maintain a defined effect [see DRUG ABUSE AND DEPENDENCE; Dependence]. ‎Symptoms of OIH include (but may not be limited to) increased levels of ‎pain upon opioid dosage increase, decreased levels of pain upon opioid ‎dosage decrease, or pain from ordinarily non-painful stimuli (allodynia). ‎These symptoms may suggest OIH only if there is no evidence of ‎underlying disease progression, opioid tolerance, opioid withdrawal, or addictive ‎behavior.‎

Cases of OIH have been reported, both with short-term and longer-term ‎use of opioid analgesics. Though the mechanism of OIH is not fully ‎understood, multiple biochemical pathways have been implicated. Medical ‎literature suggests a strong biologic plausibility between opioid ‎analgesics and OIH and allodynia. If a patient is suspected to be ‎experiencing OIH, carefully consider appropriately decreasing the dose of ‎the current opioid analgesic or opioid rotation (safely switching the ‎patient to a different opioid moiety) [see DOSAGE AND ADMINISTRATION, ‎WARNINGS].‎

Life-Threatening Respiratory Depression in Patients with Chronic Pulmonary Disease or in Elderly, Cachectic, or Debilitated Patients

The use of Nalbuphine Hydrochloride Injection in patients with acute or severe bronchial asthma in an unmonitored setting or in the absence of resuscitative equipment is contraindicated.

Patients with Chronic Pulmonary Disease:

Nalbuphine Hydrochloride Injection-treated patients with significant chronic obstructive pulmonary disease or cor pulmonale, and those with a substantially decreased respiratory reserve, hypoxia, hypercapnia, or pre-existing respiratory depression are at increased risk of decreased respiratory drive including apnea, even at recommended dosages of use of Nalbuphine Hydrochloride Injection [see WARNINGS].

Elderly, Cachectic, or Debilitated Patients:

Life-threatening respiratory depression is more likely to occur in elderly, cachectic, or debilitated patients because they may have altered pharmacokinetics or altered clearance compared to younger, healthier patients [see WARNINGS].

Monitor such patients closely, particularly when initiating and titrating Nalbuphine Hydrochloride Injection and when Nalbuphine Hydrochloride Injection is given concomitantly with other drugs that depress respiration [see WARNINGS]. Alternatively, consider the use of non-opioid analgesics in these patients.

Adrenal Insufficiency

Cases of adrenal insufficiency have been reported with opioid use, more often following greater than 1 month of use. Presentation of adrenal insufficiency may include non-specific symptoms and signs including nausea, vomiting, anorexia, fatigue, weakness, dizziness, and low blood pressure. If adrenal insufficiency is suspected, confirm the diagnosis with diagnostic testing as soon as possible. If adrenal insufficiency is diagnosed, treat with physiologic replacement doses of corticosteroids. Wean the patient off of the opioid to allow adrenal function to recover and continue corticosteroid treatment until adrenal function recovers. Other opioids may be tried as some cases reported use of a different opioid without recurrence of adrenal insufficiency. The information available does not identify any particular opioids as being more likely to be associated with adrenal insufficiency.

Severe Hypotension

Nalbuphine Hydrochloride Injection may cause severe hypotension including orthostatic hypotension and syncope in ambulatory patients. There is increased risk in patients whose ability to maintain blood pressure has already been compromised by a reduced blood volume or concurrent administration of certain CNS depressant drugs (e.g., phenothiazines or general anesthetics) [see PRECAUTIONS; Drug Interactions]. Monitor these patients for signs of hypotension after initiating or titrating the dosage of Nalbuphine Hydrochloride Injection. In patients with circulatory shock, Nalbuphine Hydrochloride Injection may cause vasodilation that can further reduce cardiac output and blood pressure. Avoid the use of Nalbuphine Hydrochloride Injection in patients with circulatory shock.

Risks of Use in Patients with Increased Intracranial Pressure, Brain Tumors, Head Injury, or Impaired Consciousness

In patients who may be susceptible to the intracranial effects of CO2 retention (e.g., those with evidence of increased intracranial pressure or brain tumors), Nalbuphine Hydrochloride Injection may reduce respiratory drive, and the resultant CO2 retention can further increase intracranial pressure. Monitor such patients for signs of sedation and respiratory depression, particularly when initiating therapy with Nalbuphine Hydrochloride Injection.

Opioids may also obscure the clinical course in a patient with a head injury. Avoid the use of Nalbuphine Hydrochloride Injection in patients with impaired consciousness or coma.

Risks of Gastrointestinal Complications

Nalbuphine Hydrochloride Injection is contraindicated in patients with known or suspected gastrointestinal obstruction, including paralytic ileus.

The nalbuphine in Nalbuphine Hydrochloride Injection may cause spasm of the sphincter of Oddi. Opioids may cause increases in serum amylase. Monitor patients with biliary tract disease, including acute pancreatitis, for worsening symptoms.

Cases of opioid-induced esophageal dysfunction (OIED) have been reported in patients taking opioids. The risk of OIED may increase as the dose and/or duration of opioids increases. Regularly evaluate patients for signs and symptoms of OIED (e.g., dysphagia, regurgitation, non-cardiac chest pain) and, if necessary, adjust opioid therapy as clinically appropriate [see CLINICAL PHARMACOLOGY].

Increased Risk of Seizures in Patients with Seizure Disorders

The nalbuphine in Nalbuphine Hydrochloride Injection may increase the frequency of seizures in patients with seizure disorders and may increase the risk of seizures occurring in other clinical settings associated with seizures. Monitor patients with a history of seizure disorders for worsened seizure control during Nalbuphine Hydrochloride Injection therapy.

Withdrawal

The use of Nalbuphine Hydrochloride Injection, a mixed agonist/antagonist opioid analgesic, in patients who are receiving a full opioid agonist analgesic may reduce the analgesic effect and/or precipitate withdrawal symptoms. Avoid concomitant use of Nalbuphine Hydrochloride Injection with a full opioid agonist analgesic.

When discontinuing Nalbuphine Hydrochloride Injection in a physically-dependent patient, gradually taper the dosage [see DOSAGE AND ADMINISTRATION]. Do not rapidly reduce or abruptly discontinue Nalbuphine Hydrochloride Injection in these patients [see DRUG ABUSE AND DEPENDENCE].

Risks of Driving and Operating Machinery

Nalbuphine Hydrochloride Injection may impair the mental or physical abilities needed to perform potentially hazardous activities such as driving a car or operating machinery. Warn patients not to drive or operate dangerous machinery unless they are tolerant to the effects of Nalbuphine Hydrochloride Injection and know how they will react to the medication [see PRECAUTIONS; Information for Patients].

Maintain patient under observation until recovered from Nalbuphine Hydrochloride Injection effects that would affect driving or other potentially dangerous tasks.

Use in Pregnancy (Other Than Labor)

Severe fetal bradycardia has been reported when Nalbuphine Hydrochloride Injection is administered during labor. Naloxone may reverse these effects. Although there are no reports of fetal bradycardia earlier in pregnancy, it is possible that this may occur. Avoid the use of Nalbuphine Hydrochloride Injection in pregnant women unless the potential benefit outweighs the risk to the fetus, and if appropriate measures such as fetal monitoring are taken to detect and manage any potential adverse effect on the fetus.

Use During Labor and Delivery

The placental transfer of nalbuphine is high, rapid, and variable with a maternal to fetal ratio ranging from 1:0.37 to 1:6. Fetal and neonatal adverse effects that have been reported following the administration of nalbuphine to the mother during labor include fetal bradycardia, respiratory depression at birth, apnea, cyanosis, and hypotonia. Some of these events have been life-threatening. Maternal administration of naloxone during labor has normalized these effects in some cases. Severe and prolonged fetal bradycardia has been reported. Permanent neurological damage attributed to fetal bradycardia has occurred. A sinusoidal fetal heart rate pattern associated with the use of nalbuphine has also been reported. Nalbuphine should be used during labor and delivery only if clearly indicated and only if the potential benefit outweighs the risk to the infant. Newborns should be monitored for respiratory depression, apnea, bradycardia and arrhythmias if nalbuphine has been used.

PRECAUTIONS

General

Impaired Renal or Hepatic Function

Because nalbuphine is metabolized in the liver and excreted by the kidneys, Nalbuphine Hydrochloride Injection should be used with caution in patients with renal or liver dysfunction and administered in reduced amounts.

Myocardial Infarction

As with all potent analgesics, Nalbuphine Hydrochloride Injection should be used with caution in patients with myocardial infarction who have nausea or vomiting.

Cardiovascular System

During evaluation of Nalbuphine Hydrochloride Injection in anesthesia, a higher incidence of bradycardia has been reported in patients who did not receive atropine pre-operatively.

Laboratory Tests

Nalbuphine Hydrochloride Injection may interfere with enzymatic methods for the detection of opioids depending on the specificity/sensitivity of the test. Consult the test manufacturer for specific details.

Information for Patients

Patients should be advised of the following information:

Addiction, Abuse, and Misuse

Inform patients that the use of Nalbuphine Hydrochloride Injection, even when ‎taken as recommended, can result in addiction, abuse, and misuse, which can lead to ‎overdose and death [see WARNINGS].‎ Instruct patients not to share Nalbuphine Hydrochloride Injection with others and to take steps to protect ‎Nalbuphine Hydrochloride Injection from theft or misuse.‎

Life-Threatening Respiratory Depression

Inform patients of the risk of life-threatening ‎respiratory depression, including information that the risk is greatest when starting ‎‎Nalbuphine Hydrochloride Injection or when the dosage is increased, and that it can occur even at recommended ‎dosages.‎

Hyperalgesia and Allodynia

Inform patients and caregivers not to increase opioid dosage without first consulting a clinician. Advise patients to inform their healthcare provider if they ‎experience symptoms of hyperalgesia, including worsening pain, increased ‎sensitivity to pain, or new pain [see WARNINGS, ADVERSE REACTIONS].‎

Serotonin Syndrome

Inform patients that opioids could cause a rare but potentially life-threatening condition resulting from concomitant administration of serotonergic drugs. Warn patients of the symptoms of serotonin syndrome and to seek medical attention right away if symptoms develop after discharge from the hospital. Instruct patients to inform their physicians if they are taking, or plan to take serotonergic medications [see PRECAUTIONS; Drug Interactions].

Monoamine Oxidase Inhibitor (MAOI) Interaction

Inform patients to avoid taking Nalbuphine Hydrochloride Injection while using any drugs that inhibit monoamine oxidase. Patients should not start MAOIs while taking Nalbuphine Hydrochloride Injection [see PRECAUTIONS; Drug Interactions].

Constipation

Advise patients of the potential for severe constipation, including management instructions and when to seek medical attention [see ADVERSE REACTIONS, CLINICAL PHARMACOLOGY].

Drug Interactions

Benzodiazepines and other Central Nervous System (CNS) Depressants

Although Nalbuphine Hydrochloride Injection possesses opioid antagonist activity, there is evidence that in nondependent patients it will not antagonize an opioid analgesic administered just before, concurrently, or just after an injection of Nalbuphine Hydrochloride Injection. Therefore, due to additive pharmacologic effects, the concomitant use of other opioid analgesics, benzodiazepines or other CNS depressants such as alcohol, non-benzodiazepine sedatives/hypnotics, anxiolytics, tranquilizers, muscle relaxants, general anesthetics, antipsychotics, gabapentinoids (gabapentin or pregabalin), and other opioids, can increase the risk of respiratory depression, profound sedation, coma, and death.

Reserve concomitant prescribing of these drugs for use in patients for whom alternative treatment options are inadequate. Limit dosages and durations to the minimum required. Monitor closely for signs of respiratory depression and sedation [see WARNINGS].

Serotonergic Drugs

The concomitant use of opioids with other drugs that affect the serotonergic neurotransmitter system, such as selective serotonin reuptake inhibitors (SSRIs), serotonin and norepinephrine reuptake inhibitors (SNRIs), tricyclic antidepressants (TCAs), triptans, 5-HT3 receptor antagonists, drugs that effect the serotonin neurotransmitter system (e.g., mirtazapine, trazodone, tramadol), certain muscle relaxants (i.e., cyclobenzaprine, metaxalone), and monoamine oxidase (MAO) inhibitors (those intended to treat psychiatric disorders and also others, such as linezolid and intravenous methylene blue), has resulted in serotonin syndrome [see PRECAUTIONS; Information for Patients].

If concomitant use is warranted, carefully observe the patient, particularly during treatment initiation and dose adjustment. Discontinue Nalbuphine Hydrochloride Injection if serotonin syndrome is suspected.

Monoamine Oxidase Inhibitors (MAOIs)

MAOI (e.g., phenelzine, tranylcypromine, linezolid) interactions with opioids may manifest as serotonin syndrome [see PRECAUTIONS; Drug Interactions] or opioid toxicity (e.g., respiratory depression, coma [see WARNINGS]). The use of Nalbuphine Hydrochloride Injection is not recommended for patients taking MAOIs or within 14 days of stopping such treatment.

If urgent use of an opioid is necessary, use test doses and frequent titration of small doses to treat pain while closely monitoring blood pressure and signs and symptoms of CNS and respiratory depression.

Muscle Relaxants

Nalbuphine may enhance the neuromuscular blocking action of skeletal muscle relaxants (e.g., cyclobenzaprine, metaxalone) and produce an increased degree of respiratory depression.

Monitor patients for signs of respiratory depression that may be greater than otherwise expected and decrease the dosage of Nalbuphine Hydrochloride Injection and/or the muscle relaxant as necessary.

Diuretics

Opioids can reduce the efficacy of diuretics by inducing the release of antidiuretic hormone.

Monitor patients for signs of diminished diuresis and/or effects on blood pressure and increase the dosage of the diuretic as needed.

Anticholinergic Drugs

The concomitant use of anticholinergic drugs may increase risk of urinary retention and/or severe constipation, which may lead to paralytic ileus.

Monitor patients for signs of urinary retention or reduced gastric motility when Nalbuphine Hydrochloride Injection is used concomitantly with anticholinergic drugs.

Carcinogenesis, Mutagenesis, Impairment of Fertility

Carcinogenesis

There was no evidence of carcinogenicity in long term animal studies were performed in rats (24 months) and mice (19 months) by oral administration at doses up to 200 mg/kg [12 times the maximum recommended human daily dose (MRHD)] and 200 mg/ per day (6 times the MRDH), respectively.

Mutagenesis

Nalbuphine Hydrochloride Injection induced an increased frequency of mutation in the mouse lymphoma assay. Nalbuphine Hydrochloride Injection did not have mutagenic activity in the Ames test with four bacterial strains, in the Chinese Hamster Ovary HGPRT assays or in the Sister Chromatid Exchange Assay. Clastogenic activity was not observed in the mouse micronucleus test or the cytogenicity bone marrow assay in rats.

Impairment of Fertility

Female rats were treated with nalbuphine hydrochloride beginning 15 days prior to mating through Lactation Day 20 via subcutaneous doses of 14, 28, or 56 mg/kg/day (0.85, 1.7, or 3.4 times the MRHD of 160 mg/day based on body surface area, respectively). Male rats were treated via oral gavage with the same nalbuphine hydrochloride doses beginning 60 days prior to and throughout mating. There were no adverse effects on either male or female fertility.

Pregnancy

Risk Summary

Use of opioid analgesics for an extended period of time during pregnancy may cause neonatal opioid withdrawal syndrome. Available data with Nalbuphine Hydrochloride Injection in pregnant women are insufficient to inform a drug-associated risk for major birth defects and miscarriage.

In animal reproduction studies, nalbuphine decreased pup survival and pup body weights when pregnant female rats were treated late in gestation and throughout lactation at 1.7 times the MRHD and when female and male rats treated either prior to mating and throughout gestation and lactation. No malformations were observed in either rats or rabbits at doses 6.1 and 3.9 times the MRHD, respectively [see Data].

The estimated background risk of major birth defects and miscarriage for the indicated population is unknown. All pregnancies have a background risk of birth defect, loss, or other adverse outcomes. In the U.S. general population, the estimated background risk of major birth defects and miscarriage in clinically recognized pregnancies is 2% to 4% and 15% to 20%, respectively.

Clinical Considerations

Fetal/Neonatal Adverse Reactions

Severe fetal bradycardia has been reported when nalbuphine hydrochloride is administered during labor. Naloxone may reverse these effects. Although there are no reports of fetal bradycardia earlier in pregnancy, it is possible that this may occur. This drug should be used in pregnancy only if clearly needed, if the potential benefit outweighs the risk to the fetus, and if appropriate measures such as fetal monitoring are taken to detect and manage any potential adverse effect on the fetus.

Labor and Delivery

The placental transfer of nalbuphine is high, rapid, and variable with a maternal to fetal ratio ranging from 1:0.37 to 1:6. Fetal and neonatal adverse effects that have been reported following the administration of nalbuphine to the mother during labor include fetal bradycardia, respiratory depression at birth, apnea, cyanosis, and hypotonia. Some of these events have been life-threatening. Maternal administration of naloxone during labor has normalized these effects in some cases. Severe and prolonged fetal bradycardia has been reported. Permanent neurological damage attributed to fetal bradycardia has occurred. A sinusoidal fetal heart rate pattern associated with the use of nalbuphine has also been reported. Nalbuphine Hydrochloride Injection should be used during labor and delivery only if clearly indicated and only if the potential benefit outweighs the risk to the infant. Newborns should be monitored for respiratory depression, apnea, bradycardia and arrhythmias if Nalbuphine Hydrochloride Injection has been used.

Opioids cross the placenta and may produce respiratory depression and psycho-physiologic effects in neonates. An opioid overdose reversal agent, such as naloxone or nalmefene, must be available for reversal of opioid-induced respiratory depression in the neonate. Nalbuphine Hydrochloride Injection is not recommended for use in pregnant women during or immediately prior to labor, when other analgesic techniques are more appropriate. Opioid analgesics, including Nalbuphine Hydrochloride Injection, can prolong labor through actions which temporarily reduce the strength, duration, and frequency of uterine contractions. However, this effect is not consistent and may be offset by an increased rate of cervical dilation, which tends to shorten labor. Monitor neonates exposed to opioid analgesics during labor for signs of excess sedation and respiratory depression.

Data

Animal Data

Pregnant rats were treated with nalbuphine hydrochloride from Gestation Day 6 to 15 via subcutaneous doses of 7, 14, or 100 mg/kg/day (0.4, 0.85, or 6.1 times the MRHD of 160 mg/day based on body surface area, respectively). There was no evidence of malformations or embryotoxicity despite reductions in maternal weight gain in the mid- and high-dose groups.

Pregnant rabbits were treated with nalbuphine hydrochloride from Gestation Day 7 to 19 via intravenous doses of 4, 8, or 32 mg/kg/day (0.5, 1, or 3.9 times the MRHD based on body surface area, respectively). There was no evidence of malformations or embryotoxicity despite reductions in maternal weight gain in the high-dose group.

Pregnant rats were treated with nalbuphine hydrochloride from Gestation Day 15 to Lactation Day 20 via subcutaneous doses of 14, 28, or 56 mg/kg/day (0.85, 1.7, or 3.4 times the MRHD based on body surface area, respectively). Pup survival was decreased in the mid- and high-dose groups and neonatal body weights were dose dependently reduced. Maternal toxicity was noted in all treatment groups (reduced body weights).

Female rats were treated with nalbuphine hydrochloride beginning 15 days prior to mating through Lactation Day 20 via subcutaneous doses of 14, 28, or 56 mg/kg/day (0.85, 1.7, or 3.4 times the MRHD of 160 mg/day based on body surface area, respectively). Male rats were treated via oral gavage with the same oxymorphone hydrochloride doses beginning 60 days prior to and throughout mating. There was reduced pup survival in the high dose group animals and reduced pup body weights in the mid- and high-dose groups.

Lactation

Limited data suggest that Nalbuphine Hydrochloride Injection is excreted in maternal milk but only in a small amount (less than 1% of the administered dose) and with a clinically insignificant effect. Infants exposed to Nalbuphine Hydrochloride Injection through breast milk should be monitored for excess sedation and respiratory depression. Withdrawal symptoms can occur in breastfed infants when maternal administration of an opioid analgesic is stopped, or when breast-feeding is stopped.

Pediatric Use

Safety and effectiveness in pediatric patients below the age of 18 years have not been established.

Geriatric Use

Elderly patients (aged 65 years or older) may have increased sensitivity to Nalbuphine Hydrochloride Injection. In general, use caution when selecting a dosage for an elderly patient, usually starting at the low end of the dosing range, reflecting the greater frequency of decreased hepatic, renal, or cardiac function and of concomitant disease or other drug therapy.

Respiratory depression is the chief risk for elderly patients treated with opioids and has occurred after large initial doses were administered to patients who were not opioid-tolerant or when opioids were co-administered with other agents that depress respiration. Titrate the dosage of Nalbuphine Hydrochloride Injection slowly in geriatric patients and frequently reevaluate the patient for signs of central nervous system ‎and respiratory depression [see WARNINGS].

Nalbuphine is known to be substantially excreted by the kidney, and the risk of adverse reactions to this drug may be greater in patients with impaired renal function. Because elderly patients are more likely to have decreased renal function, care should be taken in dose selection, and it may be useful to monitor renal function.

ADVERSE REACTIONS

The most frequent adverse reaction in 1066 patients treated in clinical studies with Nalbuphine Hydrochloride Injection was sedation 381 (36%).

Less frequent reactions were: sweaty/clammy 99 (9%), nausea/vomiting 68 (6%), dizziness/vertigo 58 (5%), dry mouth 44 (4%), and headache 27 (3%).

Other adverse reactions which occurred (reported incidence of 1% or less) were:

CNS Effects: Nervousness, depression, restlessness, crying, euphoria, floating, hostility, unusual dreams, confusion, faintness, hallucinations, dysphoria, feeling of heaviness, numbness, tingling, unreality. The incidence of psychotomimetic effects, such as unreality, depersonalization, delusions, dysphoria and hallucinations has been shown to be less than that which occurs with pentazocine.

Cardiovascular: Hypertension, hypotension, bradycardia, tachycardia.

Gastrointestinal: Cramps, dyspepsia, bitter taste.

Respiratory: Depression, dyspnea, asthma.

Dermatologic: Itching, burning, urticaria.

Miscellaneous: Speech difficulty, urinary urgency, blurred vision, flushing and warmth.

Allergic Reactions: Anaphylactic/anaphylactoid and other serious hypersensitivity reactions have been reported following the use of nalbuphine and may require immediate, supportive medical treatment. These reactions may include shock, respiratory distress, respiratory arrest, bradycardia, cardiac arrest, hypotension, or laryngeal edema. Some of these allergic reactions may be life-threatening. Other allergic‑type reactions reported include stridor, bronchospasm, wheezing, edema, rash, pruritus, nausea, vomiting, diaphoresis, weakness, and shakiness.

Postmarketing Experience

The following adverse reactions have been identified during post approval use of nalbuphine. Because these reactions are reported voluntarily from a population of uncertain size, it is not always possible to reliably estimate their frequency or establish a causal relationship to drug exposure.

Abdominal pain, pyrexia, depressed level or loss of consciousness, somnolence, tremor, anxiety, pulmonary edema, agitation, seizures, and injection site reactions such as pain, swelling, redness, burning, and hot sensations. Death has been reported from severe allergic reactions to Nalbuphine Hydrochloride Injection treatment. Fetal death has been reported where mothers received Nalbuphine Hydrochloride Injection during labor and delivery.

Serotonin Syndrome: Cases of serotonin syndrome, a potentially life-threatening condition, have been reported during concomitant use of opioids with serotonergic drugs.

Adrenal Insufficiency: Cases of adrenal insufficiency have been reported with opioid use, more often following greater than one month of use.

Hyperalgesia and Allodynia: Cases of hyperalgesia and allodynia have been ‎reported with opioid therapy of any duration [see WARNINGS]‎.

Hypoglycemia: Cases of hypoglycemia have been reported in patients ‎taking opioids. Most reports were in patients with at least one ‎predisposing risk factor (e.g., diabetes).‎

Opioid-induced esophageal dysfunction (OIED): Cases of OIED have been reported in patients taking opioids and may occur more frequently in patients taking higher doses of opioids, and/or in patients taking opioids longer term [see WARNINGS].

Adverse Reactions from Observational Studies

A prospective, observational cohort study estimated the risks of addiction, abuse, and misuse in patients initiating long-term use of Schedule II opioid analgesics between 2017 and 2021. Study participants included in one or more analyses had been enrolled in selected insurance plans or health systems for at least one year, were free of at least one outcome at baseline, completed a minimum number of follow-up assessments, and either: 1) filled multiple extended-release/long-acting opioid analgesic prescriptions during a 90‑day period (n=978); or 2) filled any Schedule II opioid analgesic prescriptions covering at least 70 of 90 days (n=1,244). Those included also had no dispensing of the qualifying opioids in the previous 6 months.

Over 12 months:

- approximately 1% to 6% of participants across the two cohorts newly met criteria for addiction, as assessed with two validated interview-based measures of moderate-to-severe opioid use disorder based on Diagnostic and Statistical Manual of Mental Disorders, Fifth Edition (DSM-5) criteria, and
- approximately 9% and 22% of participants across the two cohorts newly met criteria for prescription opioid abuse and misuse [defined in DRUG ABUSE AND DEPENDENCE], respectively, as measured with a validated self-reported instrument.

A retrospective, observational cohort study estimated the risk of opioid-involved overdose or opioid overdose-related death in patients with new long-term use of Schedule II opioid analgesics from 2006 through 2016 (n=220,249). Included patients had been enrolled in either one of two commercial insurance programs, one managed care program, or one Medicaid program for at least 9 months. New long-term use was defined as having Schedule II opioid analgesic prescriptions covering at least 70 days’ supply over the 3 months prior to study entry and none during the preceding 6 months. Patients were excluded if they had an opioid-involved overdose in the 9 months prior to study entry. Overdose was measured using a validated medical code-based algorithm with linkage to the National Death Index database. The 5-year cumulative incidence estimates for opioid-involved overdose or opioid overdose-related death ranged from approximately 1.5% to 4% across study sites, counting only the first event during follow-up. Approximately 17% of first opioid overdoses observed over the entire study period (5-11 years, depending on the study site) were fatal. Higher baseline opioid dose was the strongest and most consistent predictor of opioid-involved overdose or opioid overdose-related death. Study exclusion criteria may have selected patients at lower risk of overdose, and substantial loss to follow-up (approximately 80%) also may have biased estimates.

The risk estimates from the studies described above may not be generalizable to all patients receiving opioid analgesics, such as those with exposures shorter or longer than the duration evaluated in the studies.

DRUG ABUSE AND DEPENDENCE

Abuse

Nalbuphine Hydrochloride Injection contains nalbuphine, a substance which is subject to misuse and abuse, which can lead to the ‎development of substance use disorder, including addiction [see WARNINGS].

Misuse is the intentional use, for therapeutic purposes, of a drug by an ‎individual in a way other than prescribed by a healthcare provider or for ‎whom it was not prescribed.‎

Abuse is the intentional, non-therapeutic use of a drug, even once, for its ‎desirable psychological or physiological effects.‎

Drug addiction is a cluster of behavioral, cognitive, and physiological ‎phenomena that may include a strong desire to take the drug, difficulties ‎in controlling drug use (e.g., continuing drug use despite harmful ‎consequences, giving a higher priority to drug use than other activities ‎and obligations), and possible tolerance or physical dependence.‎

Misuse and abuse of Nalbuphine Hydrochloride Injection ‎increases risk of overdose, which ‎may lead to central nervous system and respiratory depression, ‎hypotension, seizures, and death. The risk is increased with concurrent ‎abuse of Nalbuphine Hydrochloride Injection ‎with alcohol and other CNS ‎depressants. Abuse of and addiction to opioids in some individuals may ‎not be accompanied by concurrent tolerance and symptoms of physical ‎dependence. In addition, abuse of opioids can occur in the absence of ‎addiction.‎

All patients treated with opioids require careful and frequent reevaluation ‎for signs of misuse, abuse, and addiction, because use of opioid analgesic ‎products carries the risk of addiction even under appropriate medical use. ‎Patients at high risk of Nalbuphine Hydrochloride Injection ‎abuse include those with a history ‎of prolonged use of any opioid, including products containing nalbuphine, those with a history ‎of drug or alcohol abuse, or those who use Nalbuphine Hydrochloride Injection ‎in combination ‎with other abused drugs.

“Drug-seeking” behavior is very common in persons with substance use disorders. Drug-seeking tactics include emergency calls or visits near the end of office hours, refusal to undergo appropriate examination, testing, or referral, repeated “loss” of prescriptions, tampering with prescriptions, and reluctance to provide prior medical records or contact information for other treating healthcare provider(s). “Doctor shopping” (visiting multiple prescribers to obtain additional prescriptions) is common among people who abuse drugs and people with substance use disorder. Preoccupation with achieving adequate pain relief can be appropriate behavior in a patient with inadequate pain control.

Nalbuphine Hydrochloride Injection, like other opioids, can be diverted for nonmedical use into illicit channels of distribution. Careful record-keeping of prescribing information, including quantity, frequency, and renewal requests, as required by state and federal law, is strongly advised.

Proper assessment of the patient, proper prescribing practices, periodic reevaluation of therapy, and proper dispensing and storage are appropriate measures that help to limit abuse of opioid drugs.

Risks Specific to Abuse of Nalbuphine Hydrochloride Injection

Abuse of Nalbuphine Hydrochloride Injection poses a risk of overdose and death. The risk is increased with concurrent abuse of Nalbuphine Hydrochloride Injection with alcohol and/or other CNS depressants.

Parenteral drug abuse is commonly associated with transmission of infectious diseases such as hepatitis and HIV.

Dependence

Both tolerance and physical dependence opioid therapy can develop during use of opioid therapy.

Tolerance is a physiological state characterized by a reduced response to a drug after ‎repeated administration (i.e., a higher dose of a drug is required to ‎produce the same effect that was once obtained at a lower dose).

Physical dependence is a state that develops as a result of a physiological adaptation in response ‎to repeated drug use, manifested by withdrawal signs and symptoms after ‎abrupt discontinuation or a significant dose reduction of a drug. Withdrawal may be precipitated through the administration of drugs with ‎opioid antagonist activity (e.g., naloxone, nalmefene), mixed agonist/antagonist ‎analgesics (e.g., pentazocine, butorphanol, nalbuphine), or partial agonists ‎‎(e.g., buprenorphine). Physical dependence may not occur to a clinically ‎significant degree until after several days to weeks of continued use.‎

Nalbuphine Hydrochloride Injection should not be rapidly reduced or abruptly discontinued [see DOSAGE AND ADMINISTRATION]. If Nalbuphine Hydrochloride Injection is rapidly reduced or abruptly discontinued in a physically-dependent patient, a withdrawal syndrome may occur typically characterized by restlessness, lacrimation, rhinorrhea, perspiration, chills, myalgia, and mydriasis. Other signs and symptoms also may develop, including irritability, anxiety, backache, joint pain, weakness, abdominal cramps, insomnia, nausea, anorexia, vomiting, diarrhea, or increased blood pressure, respiratory rate, or heart rate.

Infants born to mothers physically‑dependent on opioids will also be physically‑dependent and may exhibit respiratory difficulties and withdrawal signs [see PRECAUTIONS; Pregnancy].

OVERDOSAGE

Clinical Presentation

Acute overdose with Nalbuphine Hydrochloride Injection alone can be manifested by respiratory depression and dysphoria. Acute overdose with Nalbuphine Hydrochloride Injection and other opioids or CNS depressants can be manifested by respiratory depression, somnolence progressing to stupor or coma, skeletal muscle flaccidity, cold and clammy skin, constricted pupils, and, in some cases, pulmonary edema, bradycardia, hypotension, hypoglycemia, partial or complete airway obstruction, atypical snoring, and death. Marked mydriasis rather than miosis may be seen with hypoxia in overdose situations [see CLINICAL PHARMACOLOGY]. Toxic leukoencephalopathy has been reported after opioid overdose and can present hours, days, or weeks after apparent recovery from the initial intoxication.

Treatment of Overdose

In case of overdose, priorities are the reestablishment of a patent and protected airway and institution of assisted or controlled ventilation, if needed. Employ other supportive measures (including oxygen and vasopressors) in the management of circulatory shock and pulmonary edema as indicated. Cardiac arrest or arrhythmias will require advanced life-support measures.

For clinically significant respiratory or circulatory depression secondary to nalbuphine hydrochloride overdose, administer an opioid overdose reversal agent such as naloxone or nalmefene.

Because the duration of opioid reversal is expected to be less than the duration of action of nalbuphine, carefully monitor the patient until spontaneous respiration is reliably re-established. If the response to an opioid overdose reversal agent is suboptimal or only brief in nature, administer additional reversal agent as directed by the product's prescribing information.

In an individual physically‑dependent on opioids, administration of the recommended usual dosage of the reversal agent will precipitate an acute withdrawal syndrome. The severity of the withdrawal symptoms experienced will depend on the degree of physical dependence and the dose of the reversal agent administered. If a decision is made to treat serious respiratory depression in the physically‑dependent patient, administration of the reversal agent should be initiated with care and by titration with smaller than usual doses of the reversal agent.

DOSAGE AND ADMINISTRATION

Important Dosage and Administration Instructions

Nalbuphine Hydrochloride Injection should be administered as a supplement to general anesthesia only by persons specifically trained in the use of intravenous anesthetics and management of the respiratory effects of potent opioids.

An overdose reversal agent (e.g. naloxone, nalmefene), resuscitative and intubation equipment and oxygen should be readily available.

Use the lowest effective dosage for the shortest duration of time ‎consistent with individual patient treatment goals [see WARNINGS]. ‎Because the risk of overdose increases as opioid doses increase, reserve ‎titration to higher doses of Nalbuphine Hydrochloride Injection ‎for patients in whom lower ‎doses are insufficiently effective and in whom the expected benefits of ‎using a higher dose opioid clearly outweigh the substantial risks.‎

There is variability in the opioid analgesic dose and duration needed to ‎adequately manage pain due both to the cause of pain and to individual ‎patient factors. Initiate the dosing regimen for each patient individually, taking into account the patient's underlying cause and severity of pain, prior analgesic treatment and response, and risk factors for addiction, abuse, and misuse [see WARNINGS].

Respiratory depression can occur at any time during opioid therapy, ‎especially when initiating and following dosage increases with ‎Nalbuphine Hydrochloride Injection‎. Consider this risk when selecting an initial dose and when ‎making dose adjustments [see WARNINGS].‎

Parenteral drug products should be inspected visually for particulate matter and discoloration prior to administration whenever solution and container permit.

Initial Dosage

The usual recommended adult dose is 10 mg for a 70 kg individual administered subcutaneously, intramuscularly, or intravenously; this dose may be repeated every 3 to 6 hours as necessary. Use the lowest dose necessary to achieve adequate analgesia. Dosage should be adjusted according to the severity of the pain, physical status of the patient, and other medications which the patient may be receiving [see WARNINGS]. In nontolerant individuals, the recommended single maximum dose is 20 mg with a maximum total daily dose of 160 mg.

The use of Nalbuphine Hydrochloride Injection as a supplement to balanced anesthesia requires larger doses than those recommended for analgesia. Induction doses of nalbuphine hydrochloride range from 0.3 mg/kg to 3 mg/kg intravenously to be administered over a 10-to-15-minute period with maintenance doses of 0.25 to 0.5 mg/kg in single intravenous administrations as required. The use of Nalbuphine Hydrochloride Injection may be followed by respiratory depression which can be reversed with the opioid antagonist naloxone hydrochloride.

Titration and Maintenance of Therapy

Titrate the dose based upon the individual patient’s response to their initial dose of Nalbuphine Hydrochloride Injection. Individually titrate Nalbuphine Hydrochloride Injection to a dose that provides adequate analgesia and minimizes adverse reactions. Continually reevaluate patients receiving nalbuphine hydrochloride to assess the maintenance of pain control‎, signs and symptoms of opioid withdrawal,‎ and other adverse reactions, as well as to reassess for the development of addiction, abuse, or misuse [see WARNINGS]. Frequent communication is important among the prescriber, other members of the healthcare team, the patient, and the caregiver/family during periods of changing analgesic requirements, including initial titration.

If the level of pain increases after dosage stabilization, attempt to identify the source of increased pain before increasing the Nalbuphine Hydrochloride Injection dosage. If after increasing the dosage, unacceptable opioid-related adverse reactions are observed ‎(including an increase in pain after a dosage increase)‎, consider reducing the dosage‎ [see WARNINGS]. Adjust the dosage to obtain an appropriate balance between management of pain and opioid-related adverse events.

Safe Reduction and Discontinuation of Nalbuphine Hydrochloride Injection

When a patient who has been taking Nalbuphine Hydrochloride Injection regularly and may be physically‑dependent no longer requires therapy with Nalbuphine Hydrochloride Injection, taper the dose gradually, by 25% to 50% every 2 to 4 days, while regularly evaluating for signs and symptoms of withdrawal. If the patient develops these signs or symptoms, raise the dose to the previous level and taper more slowly, either by increasing the interval between decreases, decreasing the amount of change in dose, or both. Do not rapidly reduce or abruptly discontinue Nalbuphine Hydrochloride Injection in a physically-dependent patient [see WARNINGS, DRUG ABUSE AND DEPENDENCE].

HOW SUPPLIED

Nalbuphine Hydrochloride Injection is supplied as a sterile solution in single-dose ampuls and multiple‑dose fliptop vials for intramuscular, subcutaneous, or intravenous administration, and available as follows:

Unit of Sale | Concentration
NDC 0409-1463-01 | 10 mg/mL
Tray of 10 – 1 mL Single-dose Ampuls
NDC 0409-1465-01 | 20 mg/mL
Tray of 10 – 1 mL Single-dose Ampuls
NDC 0409-1464-01 | 100 mg/10 mL
Case of 25 – 10 mL Multiple-dose Fliptop Vials | (10 mg/mL)
NDC 0409-1467-01 | 200 mg/10 mL
Case of 25 – 10 mL Multiple-dose Fliptop Vials | (20 mg/mL)

STORAGE AND HANDLING

Store at 20℃ to 25°C (68℉ to 77°F). [See USP Controlled Room Temperature.]

Protect from excessive light. Store in carton until contents have been used.

Distributed by Hospira, Inc., Lake Forest, IL 60045 USA

For Medical Information about Nalbuphine Hydrochloride Injection, please visit www.pfizermedinfo.com or call 1-800-438-1985.‎

LAB-0839-13.0

Revised: 12/2025

PRINCIPAL DISPLAY PANEL - 1 mL Ampule Label - 1463

NDC 0409-1463-71

1 mL
Rx only

Nalbuphine
HCl Injection 10 mg/mL
For I.V., I.M., or S.C. Use
Protect from light.

Dist. by Hospira, Inc.
Lake Forest, IL 60045 USA

RL-7150

##-###-AA
DMMMYYYY

PRINCIPAL DISPLAY PANEL - 1 mL Ampule Tray Label - 1463

1 mL Single-dose 10 Ampuls

Rx only
NDC 0409-1463-01
Contains 10 of NDC 0409-1463-71

Nalbuphine Hydrochloride Injection
10 mg/mL

Protect from light.
Keep ampuls in tray
until time of use.

For Intravenous, Intramuscular, or Subcutaneous Use

Each mL contains nalbuphine HCl 10 mg; sodium citrate, dihydrate 0.47 mg and citric acid,
anhydrous 0.63 mg added as buffers. Sodium chloride added to adjust tonicity. May contain NaOH
and/or HCl for pH adjustment. Usual dosage: See insert. Sterile, nonpyrogenic. Discard unused
portion. Store at 20 to 25°C (68 to 77°F). [See USP Controlled Room Temperature.]

RL-7151

LOT ##-###-AA
EXP DMMMYYYY

Distributed by
Hospira, Inc., Lake Forest, IL 60045 USA

Hospira

PRINCIPAL DISPLAY PANEL - 1 mL Ampule Label - 1465

NDC 0409-1465-71

1 mL
Rx only

Nalbuphine
HCl Injection 20 mg/mL
For I.V., I.M., or S.C. Use
Protect from light.

Dist. by Hospira, Inc.
Lake Forest, IL 60045 USA

RL-7155

##-###-AA
DMMMYYYY

PRINCIPAL DISPLAY PANEL - 1 mL Ampule Tray Label - 1465

1 mL Single-dose 10 Ampuls

Rx only
NDC 0409-1465-01
Contains 10 of NDC 0409-1465-71

Nalbuphine Hydrochloride Injection
20 mg/mL

Protect from light.
Keep ampuls in tray
until time of use.

For Intravenous, Intramuscular, or Subcutaneous Use

Each mL contains nalbuphine HCl 20 mg; sodium citrate, dihydrate 0.47 mg and citric acid,
anhydrous 0.63 mg added as buffers. Sodium chloride added to adjust tonicity. May contain NaOH
and/or HCl for pH adjustment. Usual dosage: See insert. Sterile, nonpyrogenic. Discard unused
portion. Store at 20 to 25°C (68 to 77°F). [See USP Controlled Room Temperature.]

RL-7156

LOT ##-###-AA
EXP DMMMYYYY

Distributed by
Hospira, Inc., Lake Forest, IL 60045 USA

Hospira

PRINCIPAL DISPLAY PANEL - 10 mL Vial Label - 1464

NDC 0409-1464-61
Rx only

10 mL Multiple-dose

Nalbuphine
Hydrochloride Injection
100 mg/10 mL (10 mg/mL)

For I.V., I.M., or S.C. Use.

Distributed by Hospira, Inc.
Lake Forest, IL 60045 USA

Hospira

PRINCIPAL DISPLAY PANEL - 10 mL Vial Carton - 1464

1 x 10 mL
Multiple-dose
Fliptop Vial

NDC 0409-1464-61

Rx only

Nalbuphine
Hydrochloride
Injection
100 mg/10 mL
(10 mg/mL)

For Intravenous,
Intramuscular, or
Subcutaneous Use

Hospira

PRINCIPAL DISPLAY PANEL - 10 mL Vial Label - 1467

10 mL Multiple-dose

Nalbuphine HCl Injection
200 mg/10 mL (20 mg/mL)

For I.V., I.M., or S.C. Use.

Distributed by Hospira, Inc.
Lake Forest, IL 60045 USA

LOT ##-###-AA
EXP DMMMYYYY

PRINCIPAL DISPLAY PANEL - 10 mL Vial Carton - 1467

10 mL
Multi-dose Fliptop Vial

NDC 0409-1467-61
Rx only

Nalbuphine
Hydrochloride
Injection
200 mg/10 mL
(20 mg/mL)

Protect from light

For Intravenous,
Intramuscular, or
Subcutaneous Use

Hospira